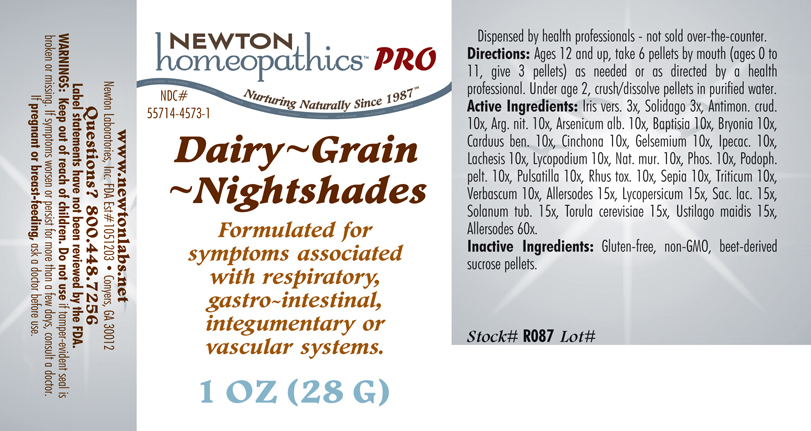 DRUG LABEL: Dairy - Grain - Nightshades 
NDC: 55714-4573 | Form: PELLET
Manufacturer: Newton Laboratories, Inc.
Category: homeopathic | Type: HUMAN PRESCRIPTION DRUG LABEL
Date: 20110601

ACTIVE INGREDIENTS: Cow Milk 60 [hp_X]/1 g; Skim Milk 60 [hp_X]/1 g; Cow Milk Fat 60 [hp_X]/1 g; Casein, Lactococcus Lactis Cultured, Aged 60 [hp_X]/1 g; Casein, Lactococcus Lactis Cultured, Penicillium Roqueforti Cultured, Aged 60 [hp_X]/1 g; Casein, Lactococcus Lactis Cultured, Penicillium Camemberti Cultured, Aged 60 [hp_X]/1 g; Barley 60 [hp_X]/1 g; Corn 60 [hp_X]/1 g; Wheat Gluten 60 [hp_X]/1 g; Oat 60 [hp_X]/1 g; White Rice 60 [hp_X]/1 g; Rye 60 [hp_X]/1 g; Wheat 60 [hp_X]/1 g; Atropa Belladonna 15 [hp_X]/1 g; Capsicum 15 [hp_X]/1 g; Solanum Dulcamara Top 15 [hp_X]/1 g; Hyoscyamus Niger 15 [hp_X]/1 g; Solanum Nigrum Whole 15 [hp_X]/1 g; Datura Stramonium 15 [hp_X]/1 g; Tobacco Leaf 15 [hp_X]/1 g; Solanum Lycopersicum 15 [hp_X]/1 g; Lactose 15 [hp_X]/1 g; Solanum Tuberosum 15 [hp_X]/1 g; Saccharomyces Cerevisiae 15 [hp_X]/1 g; Ustilago Maydis 15 [hp_X]/1 g; Antimony Trisulfide 10 [hp_X]/1 g; Silver Nitrate 10 [hp_X]/1 g; Arsenic Trioxide 10 [hp_X]/1 g; Baptisia Tinctoria Root 10 [hp_X]/1 g; Bryonia Alba Root 10 [hp_X]/1 g; Centaurea Benedicta 10 [hp_X]/1 g; Cinchona Officinalis Bark 10 [hp_X]/1 g; Gelsemium Sempervirens Root 10 [hp_X]/1 g; Ipecac 10 [hp_X]/1 g; Lachesis Muta Venom 10 [hp_X]/1 g; Sodium Chloride 10 [hp_X]/1 g; Phosphorus 10 [hp_X]/1 g; Podophyllum 10 [hp_X]/1 g; Pulsatilla Vulgaris 10 [hp_X]/1 g; Toxicodendron Pubescens Leaf 10 [hp_X]/1 g; Sepia Officinalis Juice 10 [hp_X]/1 g; Elymus Repens Root 10 [hp_X]/1 g; Verbascum Thapsus 10 [hp_X]/1 g; Iris Versicolor Root 3 [hp_X]/1 g; Solidago Virgaurea Flowering Top 3 [hp_X]/1 g; Lycopodium Clavatum Spore 10 [hp_X]/1 g
INACTIVE INGREDIENTS: Sucrose

Dairy - Grain - Nightshades

INDICATIONS & USAGE SECTION

Formulated for symptoms associated with respiratory, gastro-intestinal, integumentary or vascular systems.

DOSAGE & ADMINISTRATION SECTION

Directions: Ages 12 and up, take 6 pellets by mouth (ages 0 to 11, give 3 pellets) as needed or as directed by a health professional. Under age 2, crush/dissolve pellets in purified water.

OTC - ACTIVE INGREDIENT SECTION

Allersodes 60x, Allersodes 15x , Lycopersicum 15x, Sac. lac. 15x, Solanum tub. 15x, Torula cerevisiae 15x, Ustilago maidis 15x, Antimon. crud. 10x, Arg. nit. 10x, Arsenicum alb. 10x, Baptisia 10x, Bryonia 10x, Carduus ben. 10x, Cinchona 10x, Gelsemium 10x, Ipecac. 10x, Lachesis 10x, Lycopodium 10x, Nat. mur. 10x, Phos. 10x, Podoph. pelt.10x, Pulsatilla 10x, Rhus tox. 10x, Sepia 10x, Triticum 10x, Verbascum 10x, Iris vers. 3x, Solidago 3x.

OTC - PURPOSE SECTION

Formulated for symptoms associated with respiratory, gastro-intestinal, integumentary or vascular systems.

INACTIVE INGREDIENT SECTION

Inactive Ingredients: USP Gluten-free, non-GMO, beet-derived sucrose pellets.

QUESTIONS SECTION

www.newtonlabs.net Newton Laboratories, Inc. FDA Est # 1051203 - Conyers, GA 30012
Questions? 1.800.448.7256

WARNINGS SECTION

Warning: Keep out of reach of children. Do not use if tamper-evident seal is broken or missing. If symptoms worsen or persist for more than a few days, consult a doctor. If pregnant or breast-feeding, ask a doctor before use.

OTC - PREGNANCY OR BREAST FEEDING SECTION

If pregnant or breast-feeding, ask a doctor before use.

OTC - KEEP OUT OF REACH OF CHILDREN SECTION

Keep out of reach of children.